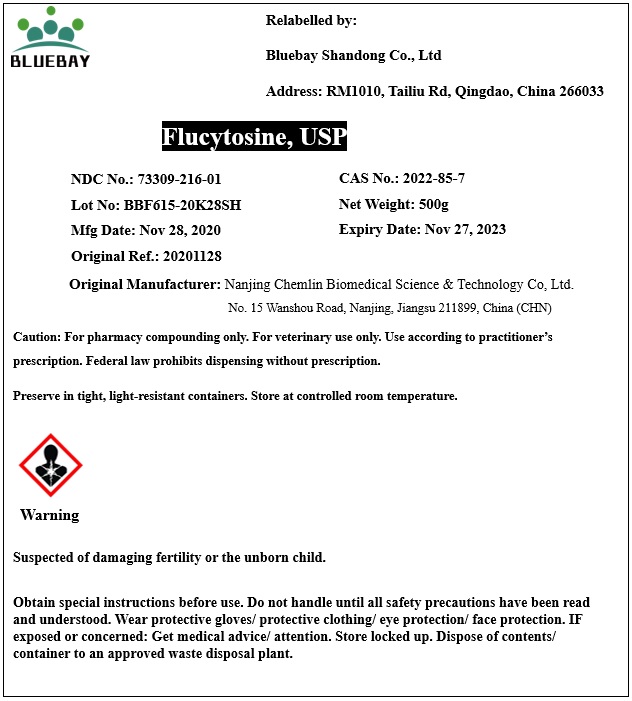 DRUG LABEL: Flucytosine
NDC: 73309-216 | Form: POWDER
Manufacturer: BLUEBAY SHANDONG CO.,LTD
Category: other | Type: BULK INGREDIENT
Date: 20201222

ACTIVE INGREDIENTS: FLUCYTOSINE 1 g/1 g

Flucytosine